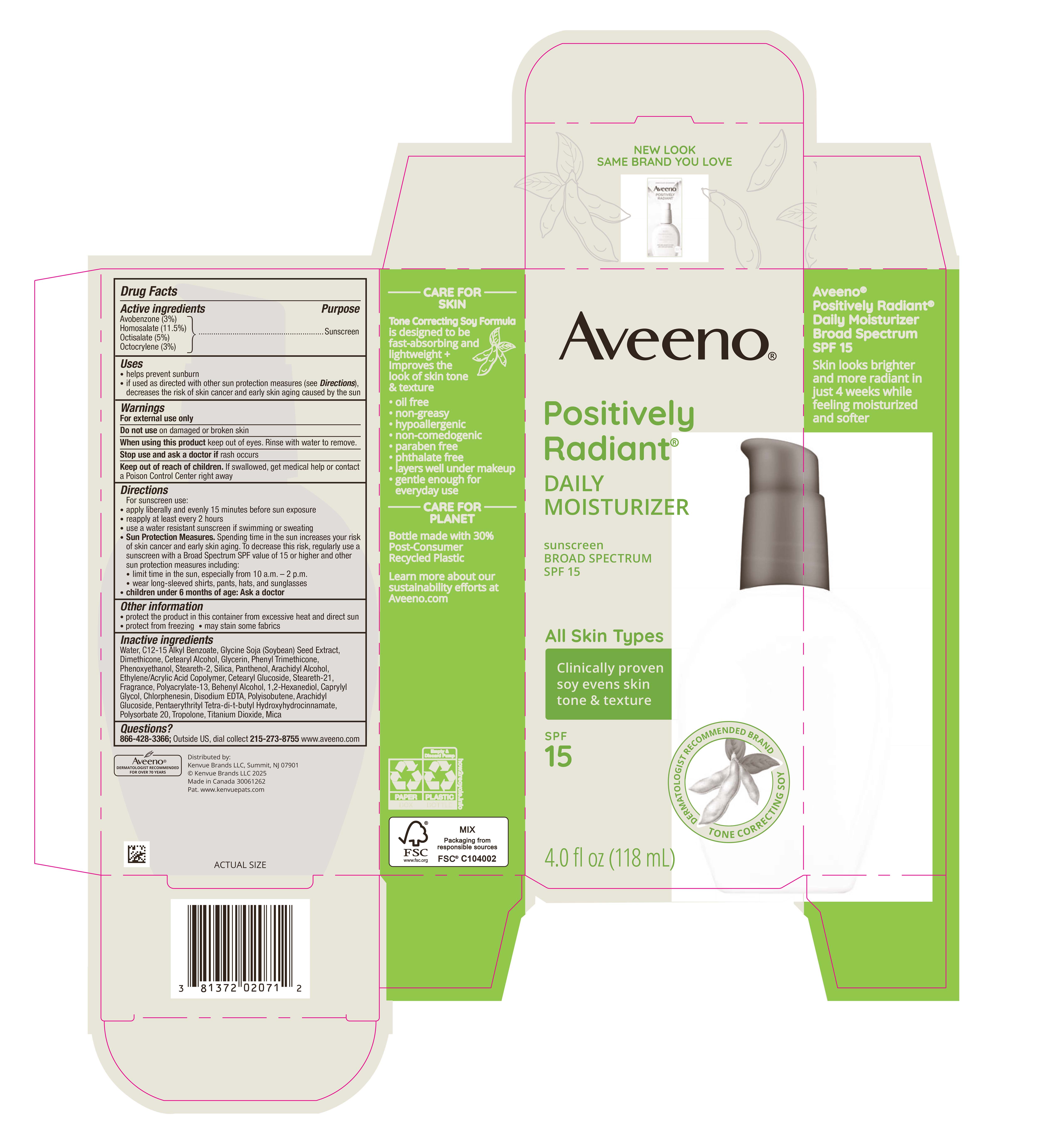 DRUG LABEL: Aveeno Positively Radiant Daily Moisturizer Sunscreen Broad Spectrum SPF 15
NDC: 69968-0760 | Form: LOTION
Manufacturer: Kenvue Brands LLC
Category: otc | Type: HUMAN OTC DRUG LABEL
Date: 20251106

ACTIVE INGREDIENTS: AVOBENZONE 30 mg/1 mL; HOMOSALATE 115 mg/1 mL; OCTISALATE 50 mg/1 mL; OCTOCRYLENE 30 mg/1 mL
INACTIVE INGREDIENTS: SOYBEAN; DIMETHICONE; CETEARYL ALCOHOL; GLYCERIN; WATER; PHENYL TRIMETHICONE; SILICON DIOXIDE; ARACHIDYL ALCOHOL; STEARETH-21; BEHENYL ALCOHOL; EDETATE DISODIUM ANHYDROUS; ARACHIDYL GLUCOSIDE; PENTAERYTHRITOL TETRAKIS(3-(3,5-DI-TERT-BUTYL-4-HYDROXYPHENYL)PROPIONATE); POLYSORBATE 20; TROPOLONE; TITANIUM DIOXIDE; MICA; ALKYL (C12-15) BENZOATE; PHENOXYETHANOL; STEARETH-2; PANTHENOL; ACRYLIC ACID/ETHYLENE COPOLYMER (600 MPA.S); CETEARYL GLUCOSIDE; 1,2-HEXANEDIOL; CAPRYLYL GLYCOL; CHLORPHENESIN; POLYACRYLATE-13

Aveeno® Positively Radiant® DAILY MOISTURIZER sunscreen BROAD SPECTRUM SPF 15

Drug Facts

ACTIVE INGREDIENT

PURPOSE

Avobenzone (3%)……………………………………………………………………………………Sunscreen

Homosalate (11.5%)………………………………………………………………………………....Sunscreen

Octisalate (5%)……………………………………………………………………………………….Sunscreen

Octocrylene (3%)……………………………………………………………………………………..Sunscreen

Use

- helps prevent sunburn
- if used as directed with other sun protection measures (see Directions), decreases the risk of skin cancer an early skin aging caused by the sun

Warnings

- For external use only

- Do not use on damaged or broken skin

- When using this product keep out of eyes. Rinse with water to remove .

- Stop use and ask a doctor if rash occurs

- Keep out of reach of children. If swallowed, get medical help or contact a Poison Control Center right away

Directions

For sunscreen use:

- apply liberally and evenly 15 minutes before sun exposure
- reapply at least every 2 hours
- use a water resistant sunscreen if swimming or sweating
- Sun Protection Measures: Spending time in the sun increases your risk of skin cancer and early skin aging . To decrease this risk, regularly use a sunscreen with a Broad Spectrum SPF value of 15 or higher and other sun protection measures including:
- limit time in the sun, especially from 10 a.m. - 2 p.m.
- wear long-sleeved shirts, pants, hats, and sunglasses
- children under 6 months of age: Ask a doctor

Other information

- protect the product in this container from excessive heat and direct sun
- protect from freezing
- may stain some fabrics

Inactive ingredients

Water, C12-15 Alkyl Benzoate, Glycine Soja (Soybean) Seed Extract, Dimethicone, Cetearyl Alcohol, Glycerin, Phenyl Trimethicone, Phenoxyethanol, Steareth-2, Silica, Panthenol, Arachidyl Alcohol, Ethylene/Acrylic Acid Copolymer, Cetearyl Glucoside, Steareth-21, Fragrance, Polyacrylate-13, Behenyl Alcohol, 1,2-Hexanediol, Caprylyl Glycol, Chlorphenesin, Disodium EDTA, Polyisobutene, Arachidyl Glucoside, Pentaerythrityl Tetra-di-t-butyl Hydroxyhydrocinnamate, Polysorbate 20, Tropolone, Titanium Dioxide, Mica

Questions?

866-428-3366; Outside US, dial collect 215-273-8755 www.aveeno.com

Distributed by:

Kenvue Brands LLC,

Summit, NJ 07901

PRINCIPAL DISPLAY PANEL - 118 mL Bottle Carton

Aveeno®

Positively

Radiant®

DAILY

MOISTURIZER

sunscreen

BROAD SPECTRUM

SPF 15

All Skin Types

Clinically proven

soy evens skin

tone & texture

SPF

15

DERMATOLOGIST RECOMMENDED BRAND

TONE CORRECTING SOY

4.0 fl oz (118 mL)